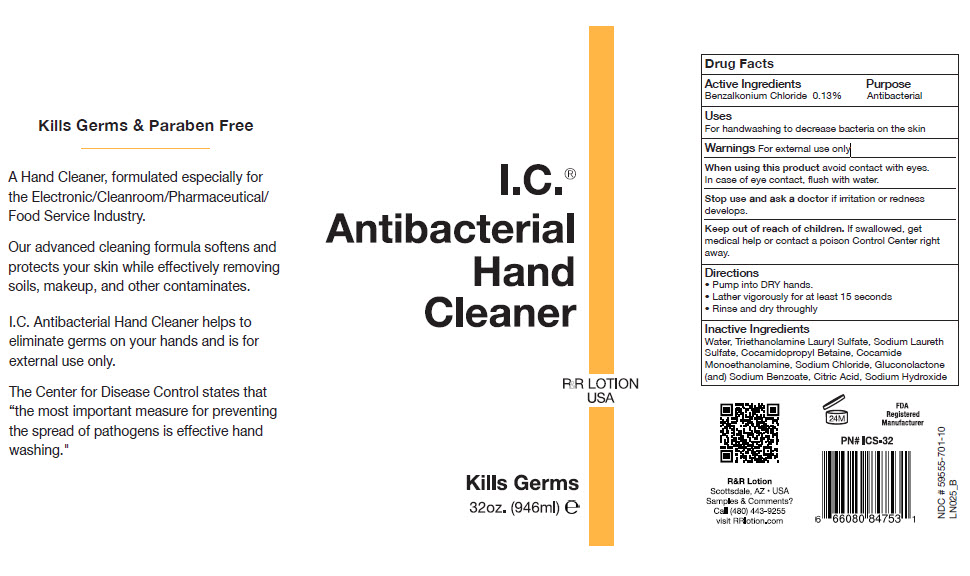 DRUG LABEL: I.C. Antibacterial Hand Cleaner
NDC: 59555-701 | Form: SOAP
Manufacturer: R & R Lotion, Inc
Category: otc | Type: HUMAN OTC DRUG LABEL
Date: 20250910

ACTIVE INGREDIENTS: Benzalkonium Chloride 1.3 mg/1 mL
INACTIVE INGREDIENTS: water; Triethanolamine Lauryl Sulfate; SODIUM LAURETH-3 SULFATE; Cocamidopropyl Betaine; COCO MONOETHANOLAMIDE; SODIUM CHLORIDE; GLUCONOLACTONE; SODIUM BENZOATE; CITRIC ACID MONOHYDRATE; SODIUM HYDROXIDE

I.C.® Antibacterial Hand Cleaner

Drug Facts

Active Ingredients

Benzalkonium Chloride 0.13%

Purpose

Antibacterial

Uses

For handwashing to decrease bacteria on the skin

Warnings

For external use only

When using this product avoid contact with eyes. In case of eye contact, flush with water.

Stop use and ask a doctor if irritation or redness develops.

Keep out of reach of children. If swallowed, get medical help or contact a poison Control Center right away.

Directions

- Pump into DRY hands.
- Lather vigorously for at least 15 seconds
- Rinse and dry throughly

Inactive Ingredients

Water, Triethanolamine Lauryl Sulfate, Sodium Laureth Sulfate, Cocamidopropyl Betaine, Cocamide Monoethanolamine, Sodium Chloride, Gluconolactone (and) Sodium Benzoate, Citric Acid, Sodium Hydroxide

PRINCIPAL DISPLAY PANEL - 946 ml Bottle Label

I.C.®
Antibacterial
Hand
Cleaner

R&R LOTION
USA

Kills Germs

32oz. (946ml) ℮